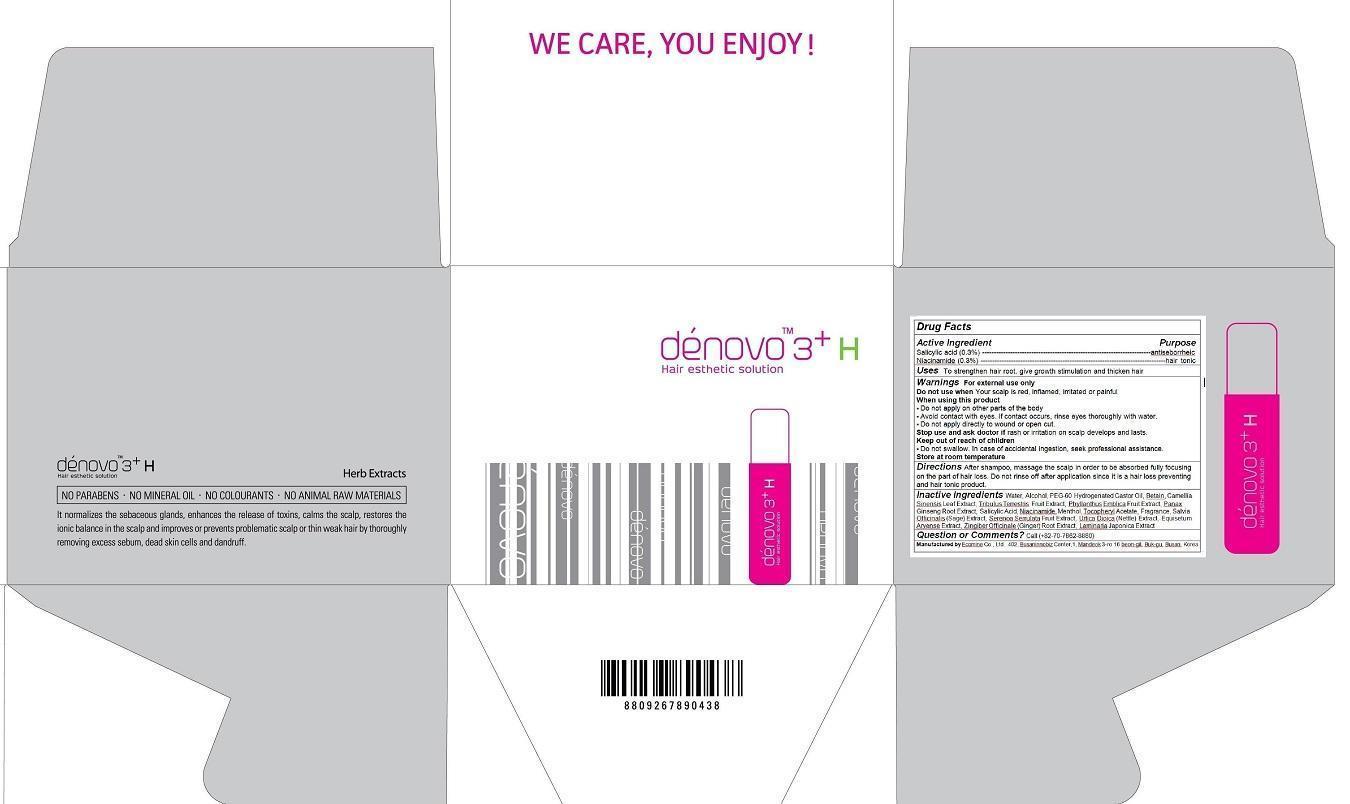 DRUG LABEL: denovo 3 H
NDC: 51270-118 | Form: LIQUID
Manufacturer: Ecomine Co., Ltd.
Category: otc | Type: HUMAN OTC DRUG LABEL
Date: 20140424

ACTIVE INGREDIENTS: Salicylic Acid 0.225 g/75 g; Niacinamide 0.225 g/75 g
INACTIVE INGREDIENTS: water; BETAINE; Alcohol; EQUISETUM ARVENSE WHOLE; SALVIA OFFICINALIS WHOLE; ZINGIBER OFFICINALE WHOLE; CAMELLIA SINENSIS WHOLE; PEG-60 HYDROGENATED CASTOR OIL; PANAX GINSENG ROOT OIL; Propylene Glycol

denovo 3+ H